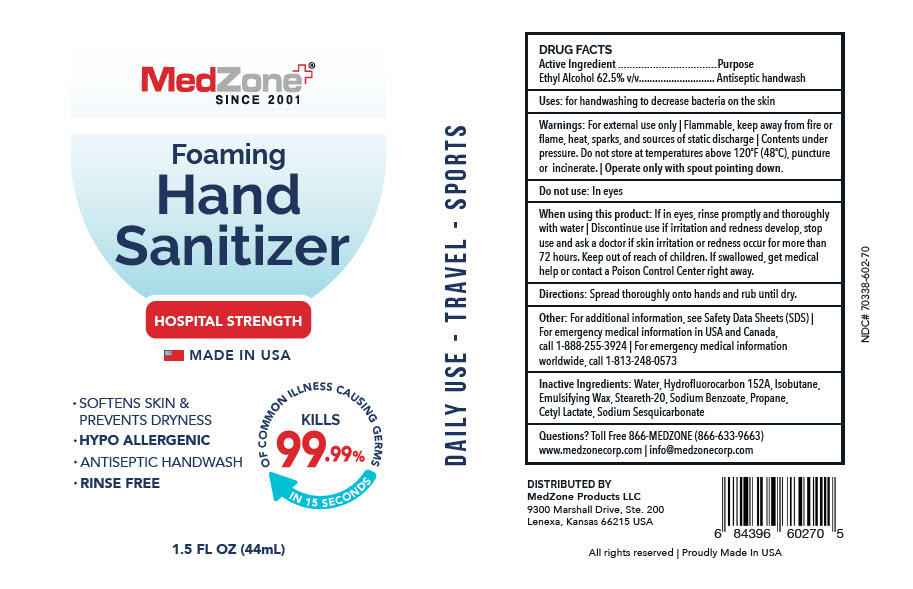 DRUG LABEL: Foaming Hand Sanitizer
NDC: 70338-602 | Form: AEROSOL, FOAM
Manufacturer: MedZone Products, LLC
Category: otc | Type: HUMAN OTC DRUG LABEL
Date: 20200527

ACTIVE INGREDIENTS: Alcohol 62.5 mL/100 mL
INACTIVE INGREDIENTS: Water; 1,1-DIFLUOROETHANE; Isobutane; Steareth-20; Sodium Benzoate; Propane; Cetyl Lactate; Sodium Sesquicarbonate

Foaming Hand Sanitizer

DRUG FACTS

Active Ingredient

Ethyl Alcohol 62.5% v/v

Purpose

Antiseptic handwash

Uses

for handwashing to decrease bacteria on the skin

Warnings

For external use only | Flammable, keep away from fire or flame, heat, sparks, and sources of static discharge | Contents under pressure. Do not store at temperatures above 120°F (48°C), puncture or incinerate. | Operate only with spout pointing down.

Do not use

In eyes

When using this product

If in eyes, rinse promptly and thoroughly with water | Discontinue use if irritation and redness develop, stop use and ask a doctor if skin irritation or redness occur for more than 72 hours.

Keep out of reach of children. If swallowed, get medical help or contact a Poison Control Center right away.

Directions

Spread thoroughly onto hands and rub until dry.

Other

For additional information, see Safety Data Sheets (SDS) | For emergency medical information in USA and Canada, call 1-888-255-3924 | For emergency medical information worldwide, call 1-813-248-0573

Inactive Ingredients

Water, Hydrofluorocarbon 152A, Isobutane, Emulsifying Wax, Steareth-20, Sodium Benzoate, Propane, Cetyl Lactate, Sodium Sesquicarbonate

Questions?

Toll Free 866-MEDZONE (866-633-9663) www.medzonecorp.com | info@medzonecorp.com

DISTRIBUTED BY
MedZone Products LLC
9300 Marshall Drive, Ste. 200
Lenexa, Kansas 66215

PRINCIPAL DISPLAY PANEL - 44 mL Can Label

MedZone®
SINCE 2001

Foaming
Hand
Sanitizer

HOSPITAL STRENGTH

MADE IN USA

- SOFTENS SKIN &
  PREVENTS DRYNESS
- HYPO ALLERGENIC
- ANTISEPTIC HANDWASH
- RINSE FREE

KILLS
99.99%
OF COMMON ILLNESS CAUSING GERMS
IN 15 SECONDS

1.5 FL OZ (44mL)